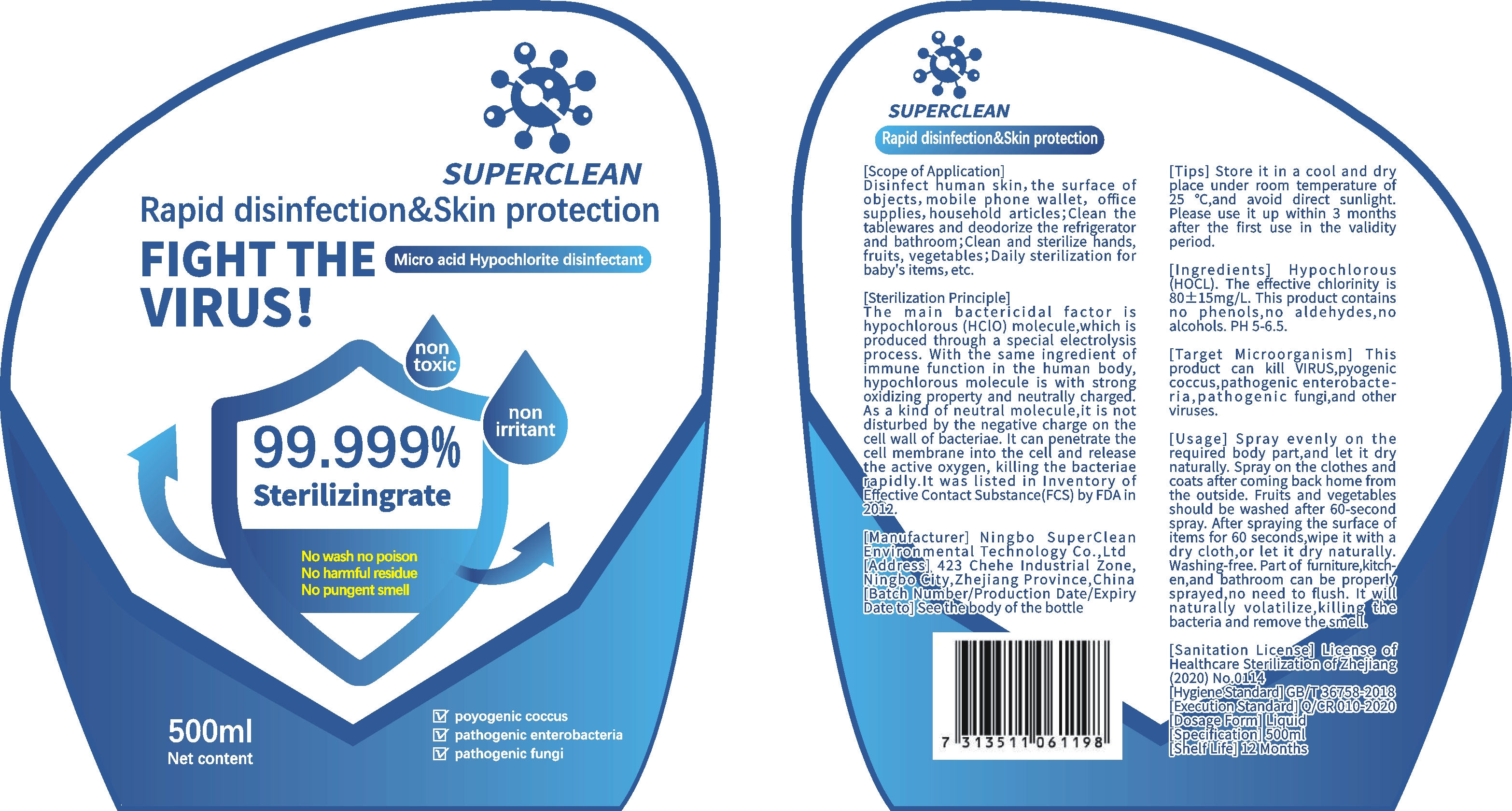 DRUG LABEL: SUPERCLEAN Micro Acid Hypochlorite Disinfectant
NDC: 54099-001 | Form: GEL
Manufacturer: NINGBO SUPERCLEAN ENVIRONMENTAL TECHNOLOGY CO., LTD.
Category: otc | Type: HUMAN OTC DRUG LABEL
Date: 20200421

ACTIVE INGREDIENTS: HYPOCHLORITE ION 0.05 mg/500 mL
INACTIVE INGREDIENTS: WATER

DOSAGE AND ADMINISTRATION

Store it in a cool and dry place under room temperature of 25。C,and avoid direct sunlight.

INACTIVE INGREDIENT

Water

INDICATIONS AND USAGE

Spray even!y, on the required body part,and let it dry naturally. Spray on the clothes and coats after coming back home from the outside. Fruits and vegetables should be washed after 60-second spray. After spraying the surface of items for 60 seconds,wipe it with a dry cloth,or let it dry naturally. Washing-free. Part of furniture,kitch-en,and bathroom can be properly sprayed,no need to flush. It wil
naturally volatilize,killing the bacteria and remove thesmell

ACTIVE INGREDIENT

Micro Acid Hypochlorite Disinfectant

keep out of children

PURPOSE

No wash no poison
No harmful residue
No pungent smell

WARNINGS

Store it in a cool and dry place under room temperature of 25。C,and avoid direct sunlight.Please use it up within 3 months after the first use in the validity period.